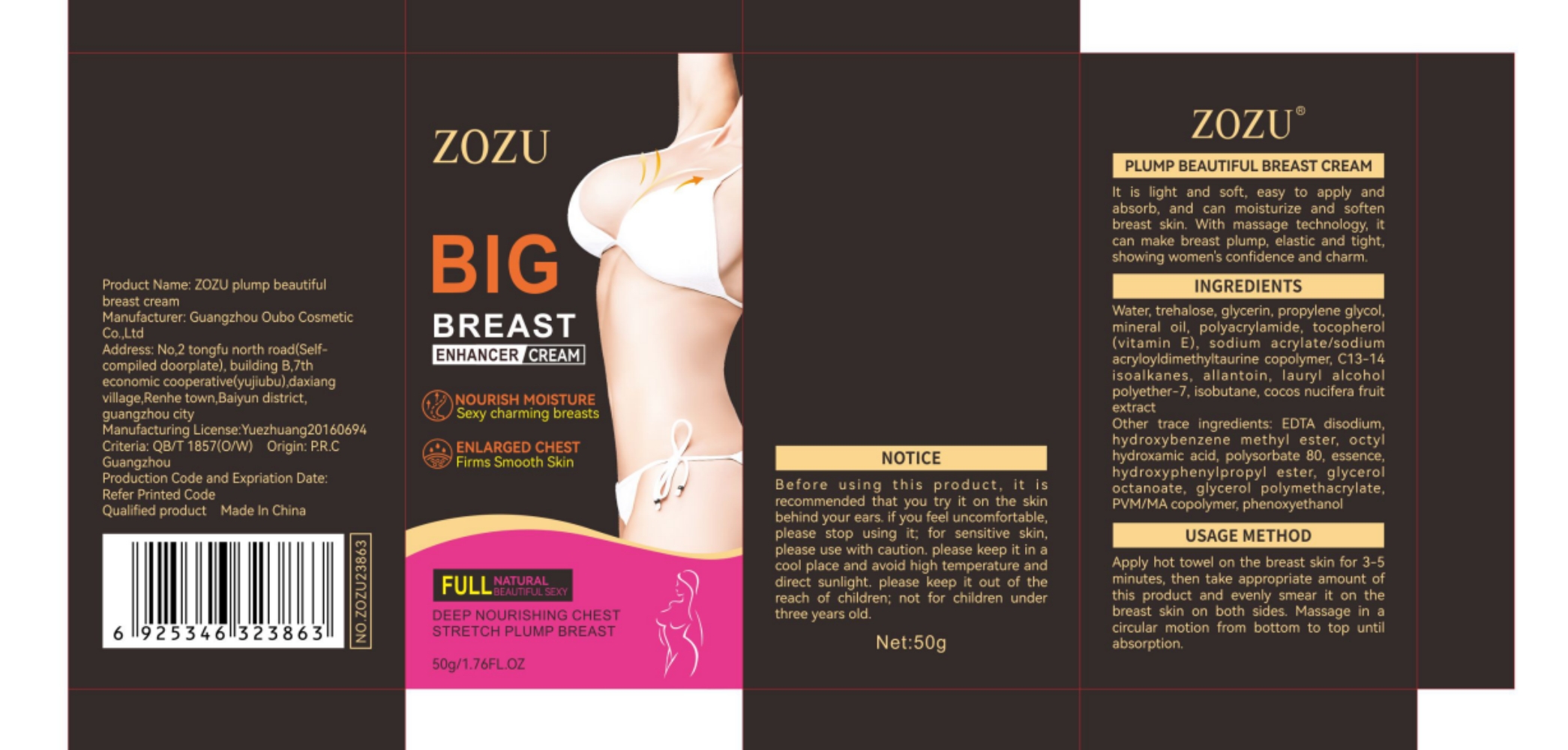 DRUG LABEL: zozu plump beautiful breast cream
NDC: 84372-047 | Form: LOTION
Manufacturer: Shenzhen Zhumeng Times Technology Co., Ltd.
Category: otc | Type: HUMAN OTC DRUG LABEL
Date: 20240904

ACTIVE INGREDIENTS: TREHALOSE 5 g/50 g
INACTIVE INGREDIENTS: LAURYL ALCOHOL; FOLIGLURAX DIHYDROCHLORIDE; EPIRUBICIN HYDROCHLORIDE; GLYCERYL CAPRYLATE; PVM/MA DECADIENE CROSSPOLYMER (58000 MPA.S); PROPYLENE GLYCOL; SODIUM; TOCOPHEROL; POLYESTER-7; COCOS NUCIFERA WHOLE; ALLANTOIN; GLYCERIN; MINERAL OIL; ACRYLATE/ISOBUTYL METHACRYLATE/N-TERT-OCTYLACRYLAMIDE COPOLYMER (75000 MW); C13-14 ISOPARAFFIN; POLYSORBATE 80; ISOBUTANE; WATER; POLYACRYLAMIDE (1500 MW); DIMETHYL ETHER; GLYCEROL, IODINATED; OCTYLHYDROQUINONE; ANISOLE

Active ingredients

trehalose 5%

Purpose

It is light and soft,easy to apply and
absorb,and can moisturize and soften
breast skin. With massage technology it
can make breast pump. elastic and tight
showing womens confidenee and charm.

Uses

Apply hot towel on the breast skin for 3-5
minutes,then take appropriate amount of
this produet and evenly smear it on the
breast skin on both sides Massage in a
circular motion from bottom to top until
absorption.

Warnings

Before using this product, it is
recommended that you try it on the skin
behind your ears if you fee uneomfortable
please stop using it for sensitive sk
please use with caution. please keep it in a
cool place and avoid high temperature and
direct sunlght. please keep it out of the
reach of children; not for children under
three years old

Dosage and administration

For external use only.

Do not use

Before using this product, it is
recommended that you try it on the skin
behind your ears if you fee uneomfortable
please stop using it for sensitive sk
please use with caution. please keep it in a
cool place and avoid high temperature and
direct sunlght. please keep it out of the
reach of children; not for children under
three years old

When using section

Apply hot towel on the breast skin for 3-5
minutes,then take appropriate amount of
this produet and evenly smear it on the
breast skin on both sides Massage in a
circular motion from bottom to top until
absorption.

stop use

Broken or inflamed body

Keep out of reach of children

If sxralowed, get medical help or contact a Poison Conirol Cenler ngiht away,

Inactive ingredients

water,glycerin,propylene glycol
mineral oil, polyacrylamide, tocopherol
(vitamin E),sodium acrylate/sodium
acryloyldimethyitaurine copolymer,C13-14
isoalkanes, allantoin,lauryl alcohol
polyether-7,isobutane,cocos nucifera fruit
extract
Other trace ingredients EDrA disodum
hydroxybenzene methyl ester, octyl
hydroxamic acid,polysorbate 80,essence
hydroxyphenylpropyl ester, glycerol
octanoate, glycerol polymethacrylate,
pvM/NiA copoymer phenoxyethanc